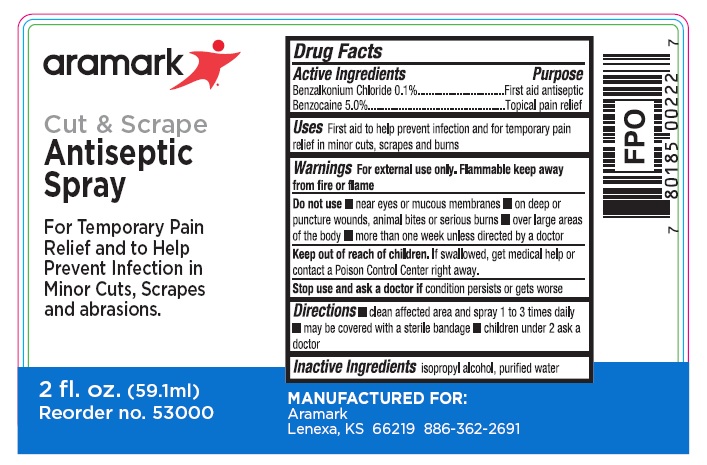 DRUG LABEL: aramark Antiseptic
NDC: 81238-5300 | Form: SPRAY
Manufacturer: Western First Aid Safety DBA Aramark
Category: otc | Type: HUMAN OTC DRUG LABEL
Date: 20210526

ACTIVE INGREDIENTS: BENZALKONIUM CHLORIDE 1.0 mg/1 mL; BENZOCAINE 50 mg/1 mL
INACTIVE INGREDIENTS: ISOPROPYL ALCOHOL; WATER

aramark Antiseptic Spray

Drug Facts

Active Ingredients

Benzalkonium Chloride 0.1%

Benzocaine 5.0%

Purpose

Benzalkonium Chloride ....First aid antiseptic

Benzocaine .................Total pain relief

Uses

First aid to help prevent infection and for temporary pain

relief in minor cuts, scrapes and burns

Warnings

For external use only.

Do not use

- near eyes or mucous membranes • on deep or

puncture wounds, animal bites, or serious burns • over large areas

of the body • more than one week unless directed by a doctor

Keep out of reach of children.

If swallowed get medical help or

contact a Poison Contrl Center right away.

Directions

• clean affected area and spray 1 to 3 times daily

• may be covered with a sterile bandage • children under 2 ask a

doctor

Inactive ingredients

isopropyl alcohol, purified water

Package Labeling

aramark

Cut & Scrape

Amtiseptic\Spray

For Temporary Pain
Relief and to Help
Prevent Infection in
Minor Cuts, Scrapes
and abrasions.

2 fl. oz. (59.1ml)
Reorder no. 53000

MANUFACTURED FOR:
Aramark
Lenexa, KS 66219 886-362-2691

res